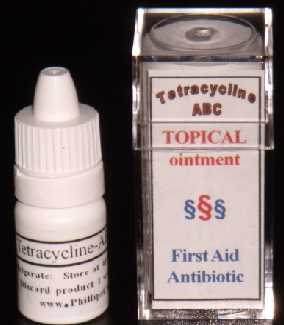 DRUG LABEL: Tetracycline-ABC
NDC: 43074-115 | Form: OINTMENT
Manufacturer: Phillips Company
Category: otc | Type: HUMAN OTC DRUG LABEL
Date: 20110215

ACTIVE INGREDIENTS: TETRACYCLINE HYDROCHLORIDE  0.03 mg/1 mL
INACTIVE INGREDIENTS: DIMETHYL SULFOXIDE; ascorbic acid; dipropylene glycol; Water; glycerin; CHLORHEXIDINE GLUCONATE; calcium gluconate; methylparaben; sodium hydroxide; sorbic acid; magnesium stearate; stearic acid; SODIUM BICARBONATE

DRUG FACTS

DRUG FACTS

Active Ingredient Purpose
Tetracycline (3%) ....................... First-aid antibiotic
Uses
First aid to help prevent skin infection in minor cuts, scrapes and burns
For external use only.
Keep away from children.
Do not use in the eyes or apply over large areas of the body.
May be harmful if swallowed.
In case of deep or puncture wounds, animal bites, or serious burns, consult a physician.
Stop use and consult a physician if the condition persists or gets worse.
Do not use if allergic to any ingredient listed on this label.
Directions
Clean the affected area. Apply a small amount of this product (an amount equal to the surface area of the tip of a finger) on the area and rub gently using a cotton swab. If not completely rubbed in after a 20-second rub-in, too much product was used. Repeat the process three times daily. Keep this product refrigerated to preserve effectiveness and color.
Other information
This product is an OTC antibiotic drug product for human use. Blended for typical skin color. May stain cloth.
Inactive ingredients
Water, glycerin, hydroxethylcellulose, chlor-hexidine gluconate, glucono delta lactone, methylparaben, sodium hydroxide, dipropylene glycol, dimethyl sulfoxide, sorbic acid, ascorbic acid, magnesium stearate, stearic acid.
Side effects
Same as other tetracycline products.
See listing of side effects online at
www.PhillipsCompany.4T.com/CC.pdf
Report any side effects to Phillips Company,
311 Chickasaw Street, Millerton, OK USA 74750
Tel. 580-746-2430.
Email: PhillipsCompany@cox.net

ACTIVE INGREDIENTS

Active Ingredient Purpose
Tetracycline (3%) ....................... First-aid antibiotic

ASK DOCTOR

In case of deep or puncture wounds, animal bites, or serious burns, consult a physician.
Stop use and consult a physician if the condition persists or gets worse.

DO NOT USE

For external use only.
Keep away from children.
Do not use in the eyes or apply over large areas of the body.
May be harmful if swallowed.
Do not use if allergic to any ingredient listed on this label.

CHILDREN

Keep away from children.

PURPOSE

Active Ingredient Purpose
Tetracycline (3%) ....................... First-aid antibiotic

STOP USE

Stop use and consult a physician if the condition persists or gets worse.

Do not use if allergic to any ingredient listed on this label.

WHEN USING

First aid to help prevent skin infection in minor cuts, scrapes and burns
In case of deep or puncture wounds, animal bites, or serious burns, consult a physician.

WARNINGS

Side effects: same as other tetracycline products.
See listing of side effects online at www.PhillipsCompany.4T.com/CC.pdf
Report any side effects to Phillips Company, 311 Chickasaw Street, Millerton, OK USA 74750
Tel. 580-746-2430. Email: PhillipsCompany@cox.net

DOSAGE & ADMINISTRATION

Clean the affected area. Apply a small amount of this product (an amount equal to the surface area of the tip of a finger) on the area and rub gently using a cotton swab. If not completely rubbed in after a 20-second rub-in, too much product was used. Repeat the process three times daily. For best results, refrigerate this product to reduce oxidation rate; to preserve effectiveness and color (normally orange). Discard this product if color turns black.

USE

First aid to help prevent skin infection in minor cuts, scrapes and burns
For external use only.
Keep away from children.
Do not use in the eyes or apply over large areas of the body.
May be harmful if swallowed.
In case of deep or puncture wounds, animal bites, or serious burns, consult a physician.
Stop use and consult a physician if the condition persists or gets worse.
Do not use if allergic to any ingredient listed on this label.

INACTIVE INGREDIENTS

Water, glycerin, hydroxethylcellulose, chlorhexidine gluconate, glucono delta lactone, methylparaben, sodium hydroxide, dipropylene glycol, dimethyl sulfoxide, sorbic acid, ascorbic acid, magnesium stearate, stearic acid, sodium bicarbonate.